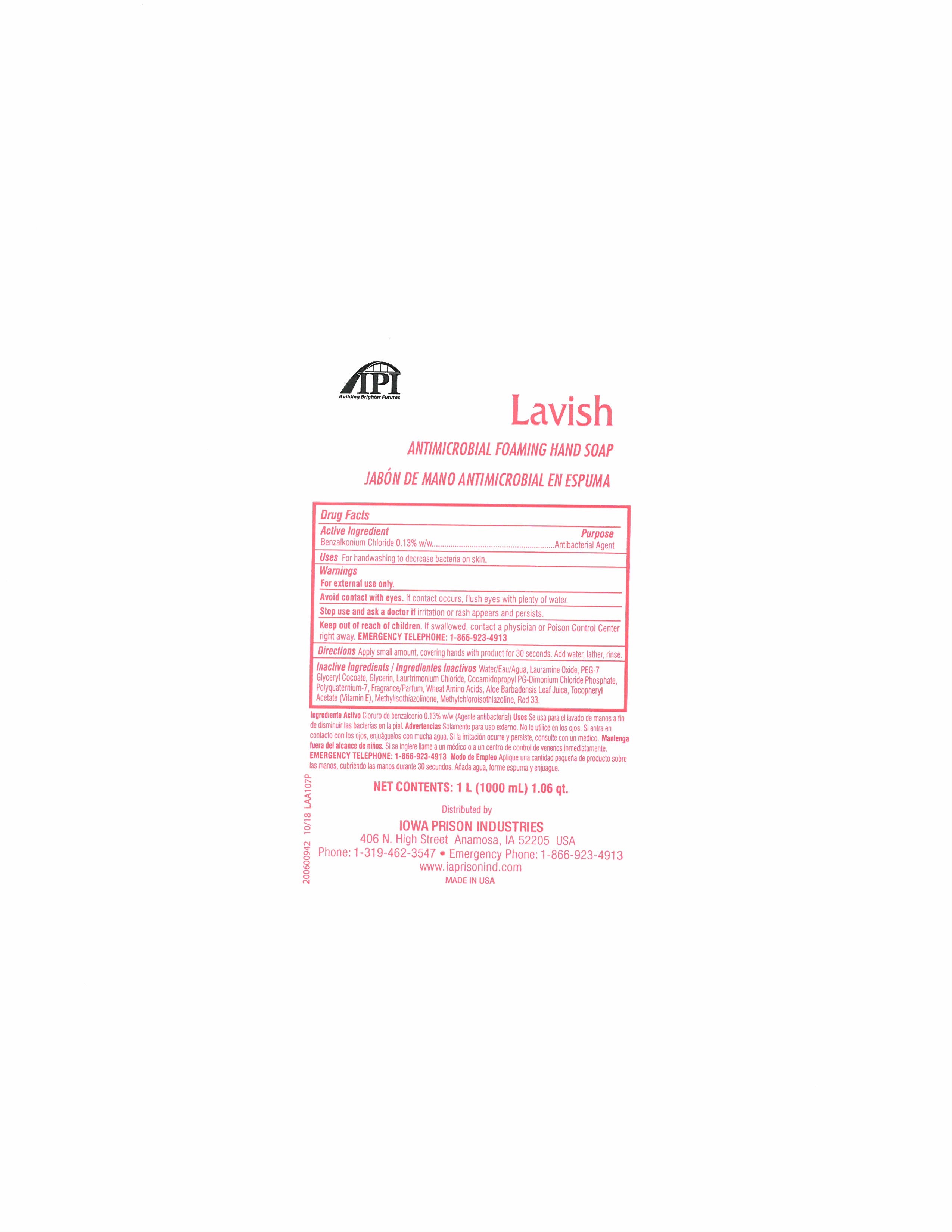 DRUG LABEL: Foaming Antibacterial Hand
NDC: 61307-640 | Form: SOAP
Manufacturer: US Chemical Corporation
Category: otc | Type: HUMAN OTC DRUG LABEL
Date: 20230824

ACTIVE INGREDIENTS: BENZALKONIUM CHLORIDE 0.013 mg/1 mL
INACTIVE INGREDIENTS: PEG-7 GLYCERYL COCOATE; GLYCERIN; SODIUM COCOYL WHEAT AMINO ACIDS; METHYLCHLOROISOTHIAZOLINONE; .ALPHA.-TOCOPHEROL ACETATE, D-; LAURTRIMONIUM CHLORIDE; COCAMIDOPROPYL PG-DIMONIUM CHLORIDE PHOSPHATE; POLYQUATERNIUM-7 (70/30 ACRYLAMIDE/DADMAC; 1600 KD); WATER; ALOE VERA LEAF; METHYLISOTHIAZOLINONE; LAURAMINE OXIDE

US Chem F640F

DOSAGE AND ADMINISTRATION

Directions Apply a small amount , covering hands with product for 30 seconds. Add water, lather and rinse.

INACTIVE INGREDIENT

Inactive Ingredients Water, Lauramine Oxide, PEG-7 Glyceryl Cocate, Glycerin, Laurtrimonium Chloride, Cocamidopropyl PG-Dimonium Chloride Phosphate, Polyquaternium-7, Fragrance, Wheat Amono Acid, Aloe Barbadensis Leaf Juice, Tocopheryl Acetate, Methylisothiazolinone, Methylchloroisothiazolinone.

INDICATIONS AND USAGE

Uses For handwashing to decrease bacteria on skin.

Active Ingredient Benzalkonium Chloride 0.13% w/w

Keep out of reach of children. If swallowed, contact a physician or Poison Control Center right away.

Purpose Antibacterial Agent

WARNINGS

Warnings For external use only. Avoid contact with eyes. If contact occurs, flush eyes with plenty of water. Stop use and ask a doctor if irritation or rash appears and persists.